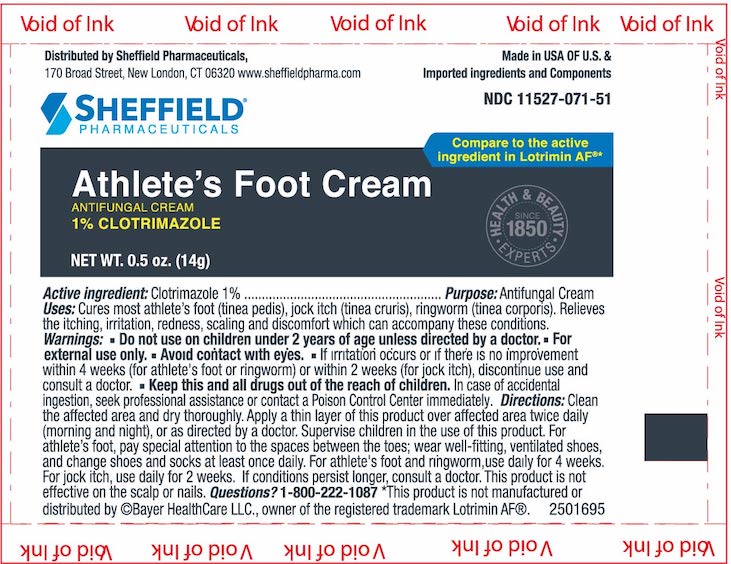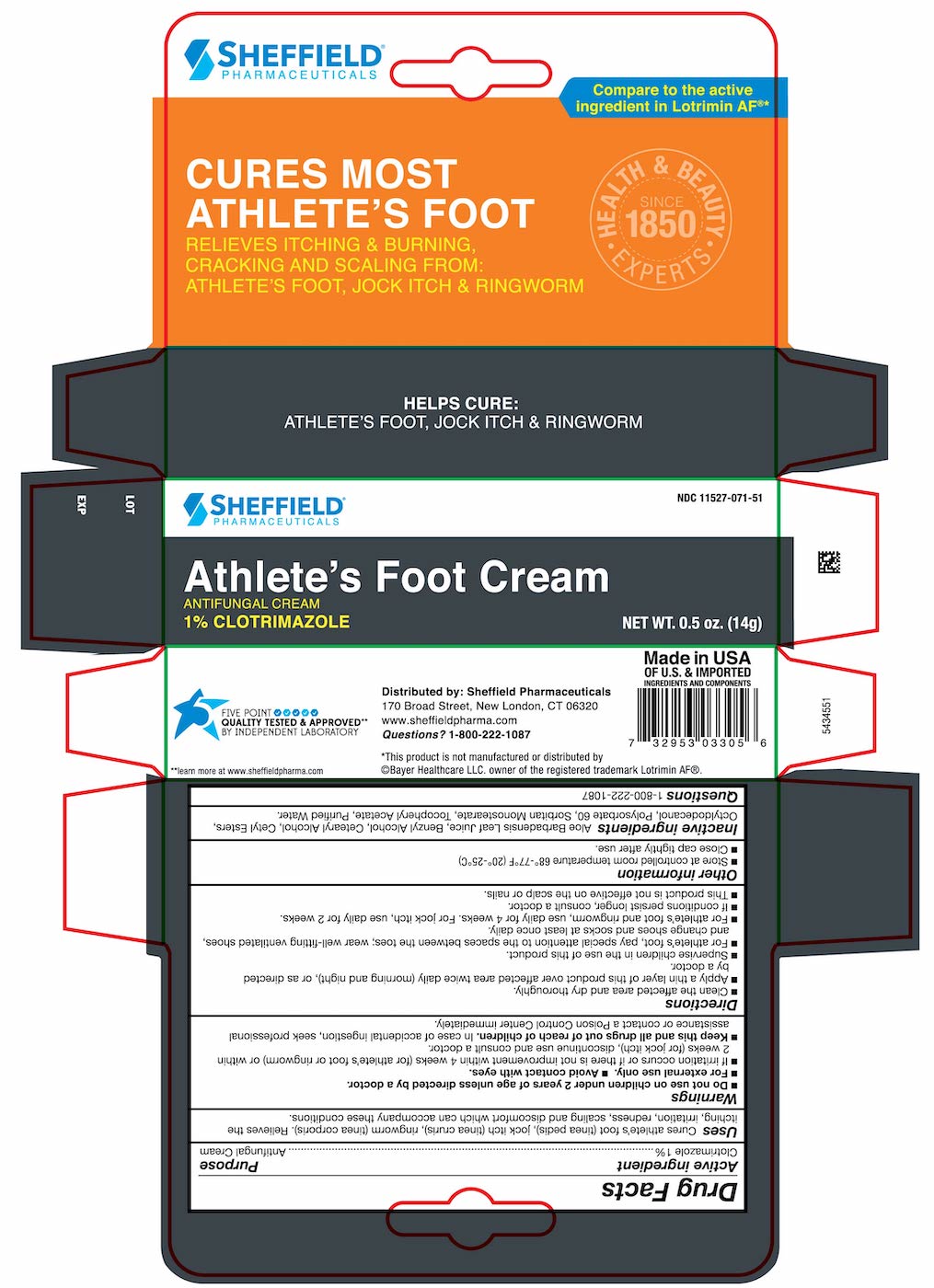 DRUG LABEL: Dr Sheffield Athletes Foot
NDC: 11527-071 | Form: CREAM
Manufacturer: Sheffield Pharmaceuticals LLC
Category: otc | Type: HUMAN OTC DRUG LABEL
Date: 20250219

ACTIVE INGREDIENTS: CLOTRIMAZOLE 10 mg/1 g
INACTIVE INGREDIENTS: WATER; CETOSTEARYL ALCOHOL; POLYSORBATE 60; BENZYL ALCOHOL; SORBITAN MONOSTEARATE; .ALPHA.-TOCOPHEROL ACETATE; ALOE VERA LEAF; OCTYLDODECANOL; CETYL PALMITATE

Sheffield Clotrimazole Cream

Drug Facts

Active ingredient

Clotrimazole 1 %

Purpose

Antifungal Cream

Uses

Cures athlete's foot (tinea pedis), jock itch (tinea cruris), ringworm (tinea corporis). Relieves the itching, irritation, redness, scaling and discomfort which can accompany these conditions.

Warnings

- Do not use on children under 2 years of age unless directed by a doctor.
- For external use only.
- Avoid contact with eyes.
- If irritation occurs or if there is not improvement within 4 weeks (for athlete's foot or ringworm) or within 2 weeks (for jock itch), discontinue use and consult a doctor.

KEEP OUT OF REACH OF CHILDREN

- Keep this and all drugs out of reach of children. In case of accidental ingestion, seek professional assistance or contact a Poison Control Center immediately.

Directions

- Clean the affected area and dry thoroughly.
- Apply a thin layer of this product over affected area twice daily (morning and night), or as directed by a doctor.
- Supervise children in the use of this product.
- For athlete's foot, pay special attention to the spaces between the toes; wear well-fitting, ventilated shoes, and change shoes and socks at least once daily.
- For athlete's foot and ringworm, use daily for 4 weeks. For jock itch, use daily for 2 weeks.
- If conditions persist longer, consult a doctor.
- This product is not effective on the scalp or nails.

Other information

- Store at controlled room temperature 68°-77°F (20°-25°C).
- Close cap tightly after use.

Inactive ingredients

Aloe Barbadensis Leaf Juice, Benzyl Alcohol, Cetearyl Alcohol, Cetyl Esters, Octyldodecanol, Polysorbate 60, Sorbitan Monostearate, Tocopheryl Acetate, Purified Water.

Questions

1-800-222-1087

Principal Display Panel – 0.5 OZ Tube

Sheffield NDC 11524-071-51

Athlete's
Foot Cream

Antifungal Cream

Clotrimazole 1%

Helps cure: • Athlete's Foot • Jock Itch • Ringworm

Made in the USA

NET WT. 0.5 OZ (14 g)

Principal Display Panel – 0.5OZ Carton

Principal Display Panel – 0.5 OZ Carton

Sheffield NDC 11524-071-51

Athlete's
Foot Cream

Antifungal Cream

Clotrimazole 1%

Helps cure: • Athlete's Foot • Jock Itch • Ringworm

Made in the USA

NET WT. 0.5oz (14g)